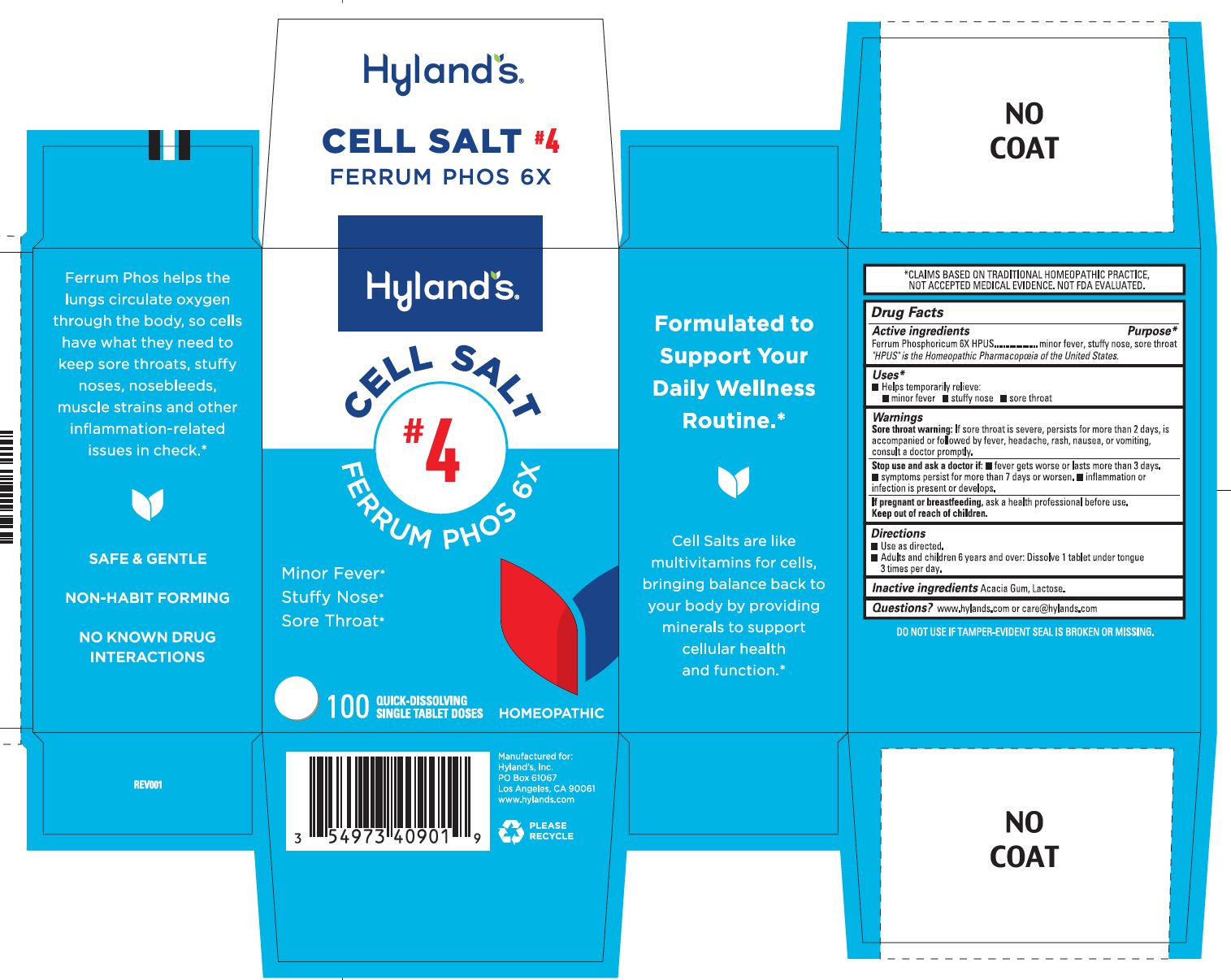 DRUG LABEL: Ferrum Phos 6X
NDC: 54973-4090 | Form: TABLET, SOLUBLE
Manufacturer: Hyland's Inc.
Category: homeopathic | Type: HUMAN OTC DRUG LABEL
Date: 20250325

ACTIVE INGREDIENTS: FERROSOFERRIC PHOSPHATE 6 [hp_X]/1 1
INACTIVE INGREDIENTS: LACTOSE MONOHYDRATE; ACACIA

Cell Salt #4 Ferrum Phos 6X

PURPOSE

Minor Fever

Stuffy Nose

Sore Throat

Drug Facts

Active ingredients | Purpose
Ferrum Phosphoricum 6X HPUS | minor fever, stuffy nose, sore throat

"HPUS" is the Homeopathic Pharmacopoeia of the United States.

Uses

■ Temporarily relieves:
■ minor fever ■ stuffy nose ■ sore throat

Warnings

Sore throat warning

If sore throat is severe, persists for more than 2 days, is accompanied or followed by fever, headache, rash, nausea, or vomiting,
consult a doctor promptly.

Stop use and ask a doctor if

■ fever gets worse or lasts more than 3 days. ■ symptoms persist for more than 7 days or worsen. ■ inflammation or infection is present or develops.

If pregnant or breastfeeding

Ask a health professional before use.

Directions

■ Use as directed.
■ Adults and children 6 years and over: Dissolve 1 tablet under tongue
3 times per day.

Inactive ingredients

Acacia Gum, Lactose.

Questions?

www.hylands.com or care@hylands.com

PACKAGE LABEL - 100 TABLETS BOTTLE CARTON

Hyland's

NATURALS™

CELL SALT

#4

FERRUM PHOS 6X

Minor Fever*

Stuffy Nose*

Sore Throat*

100

QUICK-DISSOLVING

SINGLE TABLET DOSES

HOMEOPATHIC